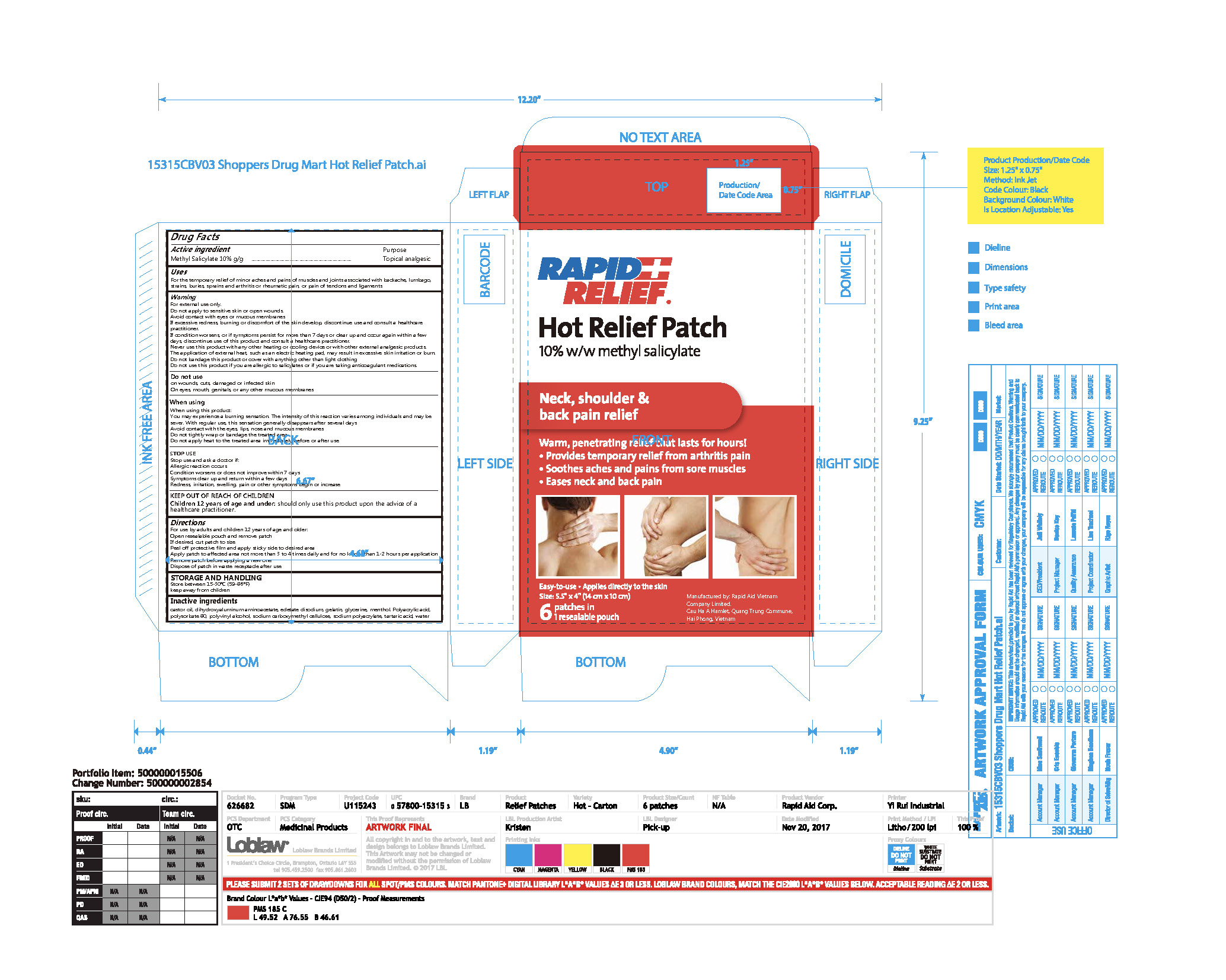 DRUG LABEL: Rapid Relief Hot Relief Patch
NDC: 83569-003 | Form: PATCH
Manufacturer: RAPID AID VIET NAM CO., LTD
Category: otc | Type: HUMAN OTC DRUG LABEL
Date: 20251016

ACTIVE INGREDIENTS: METHYL SALICYLATE 10 g/100 g
INACTIVE INGREDIENTS: MENTHOL; CASTOR OIL; GELATIN; TARTARIC ACID; POLYSORBATE 80; POLYVINYL ALCOHOL, UNSPECIFIED; POLYACRYLIC ACID (450000 MW); GLYCERIN; WATER; EDETATE DISODIUM; SODIUM POLYACRYLATE (8000 MW); DIHYDROXYALUMINUM AMINOACETATE; CARBOXYMETHYLCELLULOSE SODIUM, UNSPECIFIED

Active Ingredient(s)

Methyl Salicylate 10% w/w.

Purpose

Topical analgesic

Use

For the temporary relief of minor aches and pains of muscles and joints associated with backache, lumbago, strains, buries, sprains and arthritis or rheumatic pain, or pain of tendons and ligaments.

Warnings

For external use only.
Do not apply to sensitive skin or open wounds.
Avoid contact with eyes or mucous membranes
If excessive redness, burning or discomfort of the skin develop, discontinue use and consult a healthcare practitioner.
If condition worsens, or if symptoms persist for more than 7 days or clear up and occur again within a few days, discontinue use of this product and consult a healthcare practitioner.
Never use this product with any other heating or cooling device or with other external analgesic products.
The application of external heat, such as an electric heating pad, may result in excessive skin irritation or burn.
Do not bandage this product or cover with anything other than light clothing
Do not use this product if you are allergic to salicylates or if you are taking anticoagulant medications.

Do not use

on wounds, cuts, damaged or infected skin
On eyes, mouth, genitals, or any other mucous membranes

When using this product:

You may experience a burning sensation. The intensity of this reaction varies among individuals and may be sever. With regular use, this sensation generally disappears after several days.
Avoid contact with the eyes, lips, nose and mucous membranes
Do not tightly wrap or bandage the treated area
Do not apply heat to the treated area immediately before or after use

Stop use and ask a doctor if:

Allergic reaction occurs
Condition worsens or does not improve within 7 days
Symptoms clear up and return within a few days
Redness, irritation, swelling, pain or other symptoms begin or increase

KEEP OUT OF REACH OF CHILDREN

Children 12 years of age and under: should only use this product upon the advice of a healthcare practitioner.

Directions

For use by adults and children 12 years of age and older:
Open resealable pouch and remove patch
If desired, cut patch to size
Peel off protective film and apply sticky side to desired area
Apply patch to affected area not more than 3 to 4 times daily and for no longer than 1-2 hours per application
Remove patch before applying a new one
Dispose of patch in waste receptacle after use

STORAGE AND HANDLING

Store between 15-30℃(59-86℉) keep away from children

Inactive ingredients

castor oil, dihydroxyaluminum aminoacetate, edetate disodium, gelatin, glycerine, menthol. Polyacrylic acid, polysorbate 80, polyvinyl alcohol, sodium carboxymethyl cellulose, sodium polyacrylate, tartaric acid, water